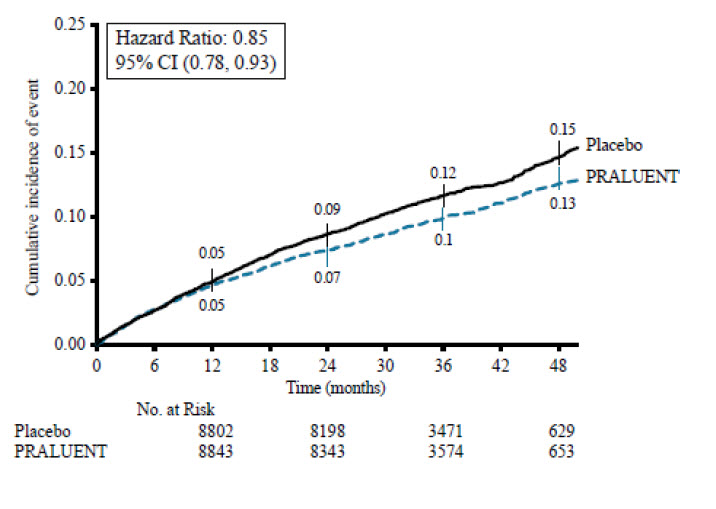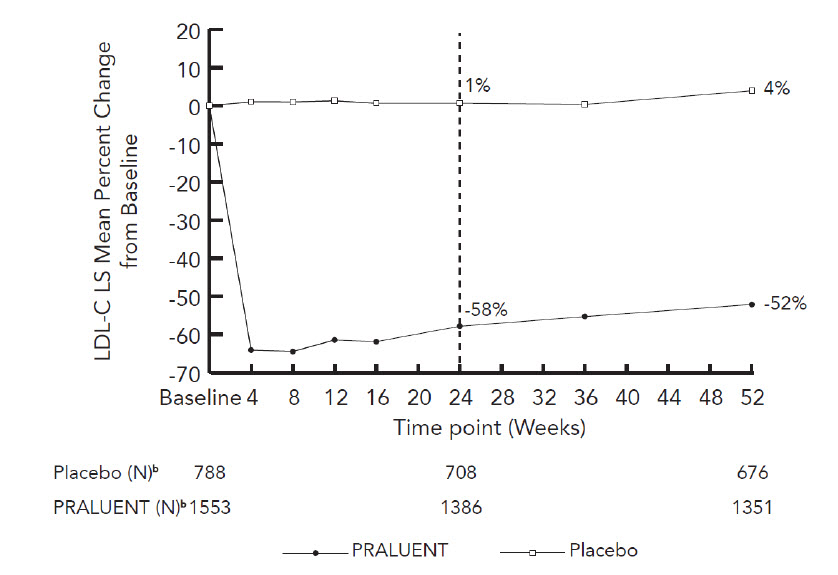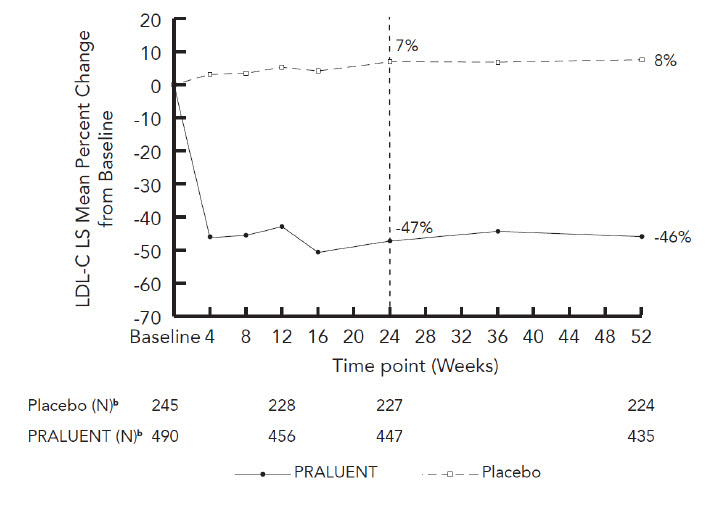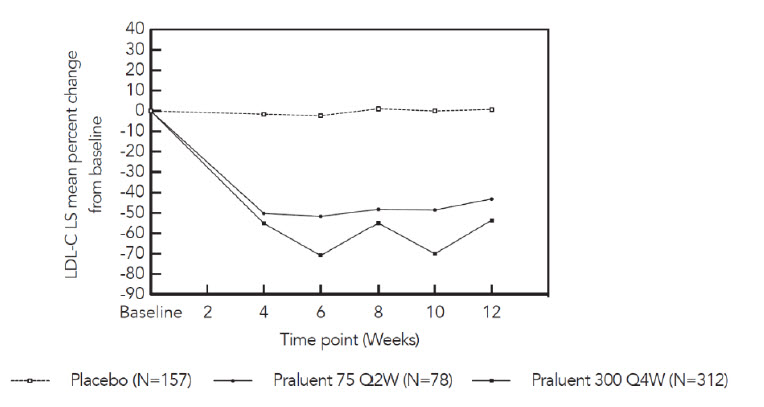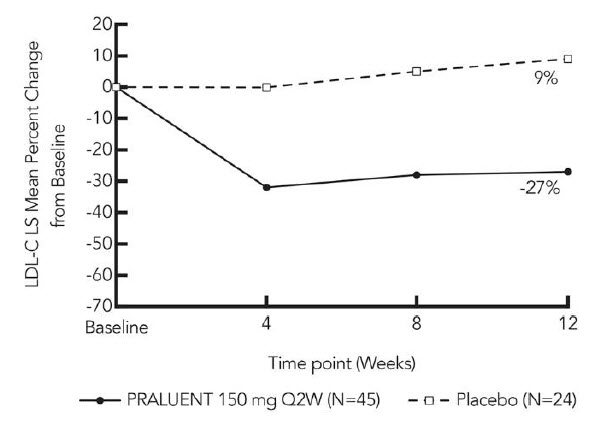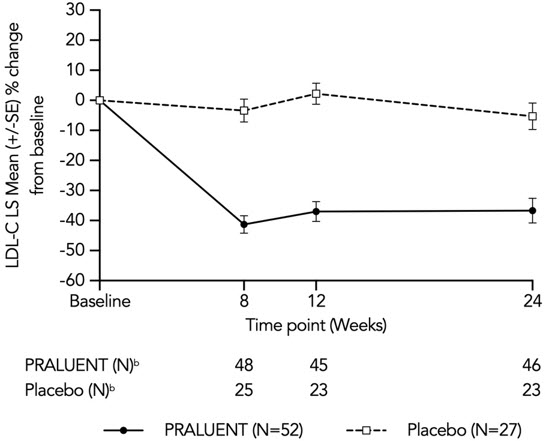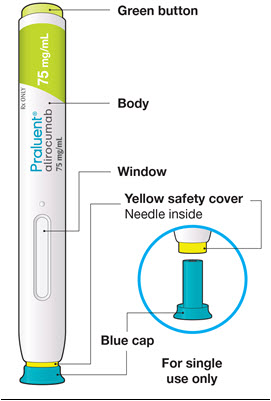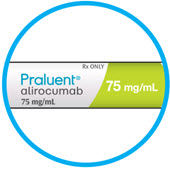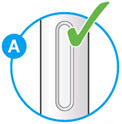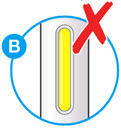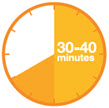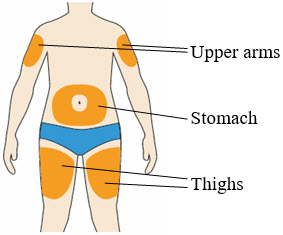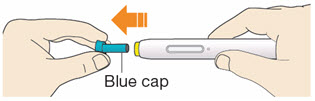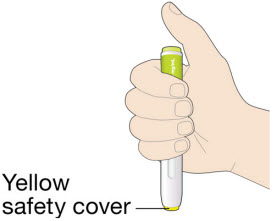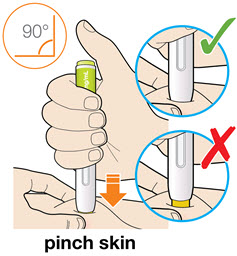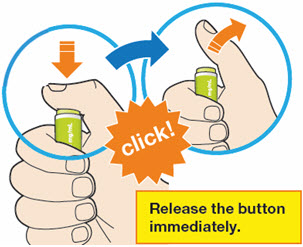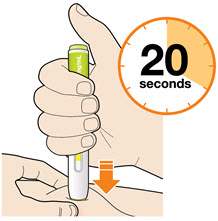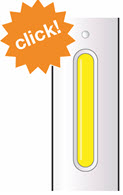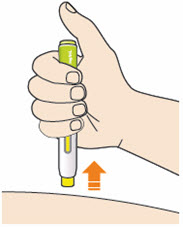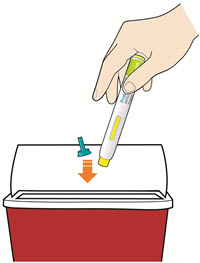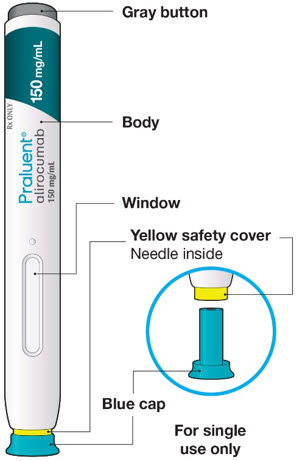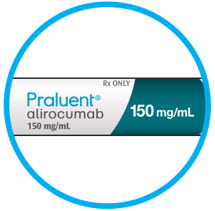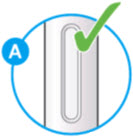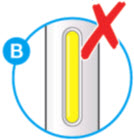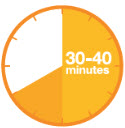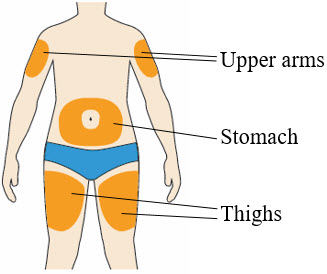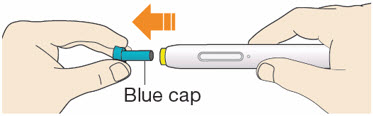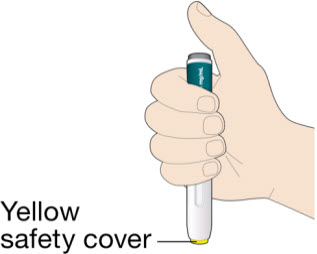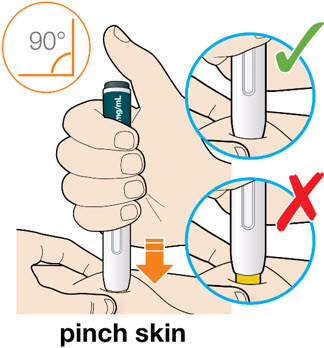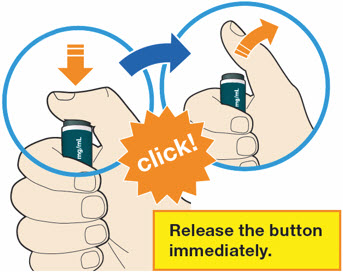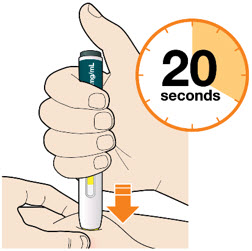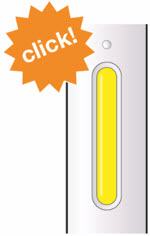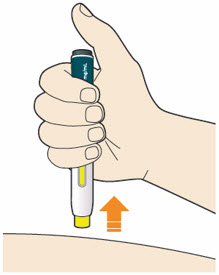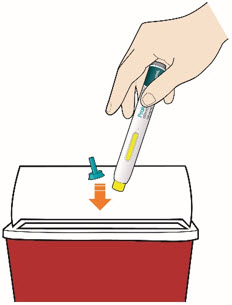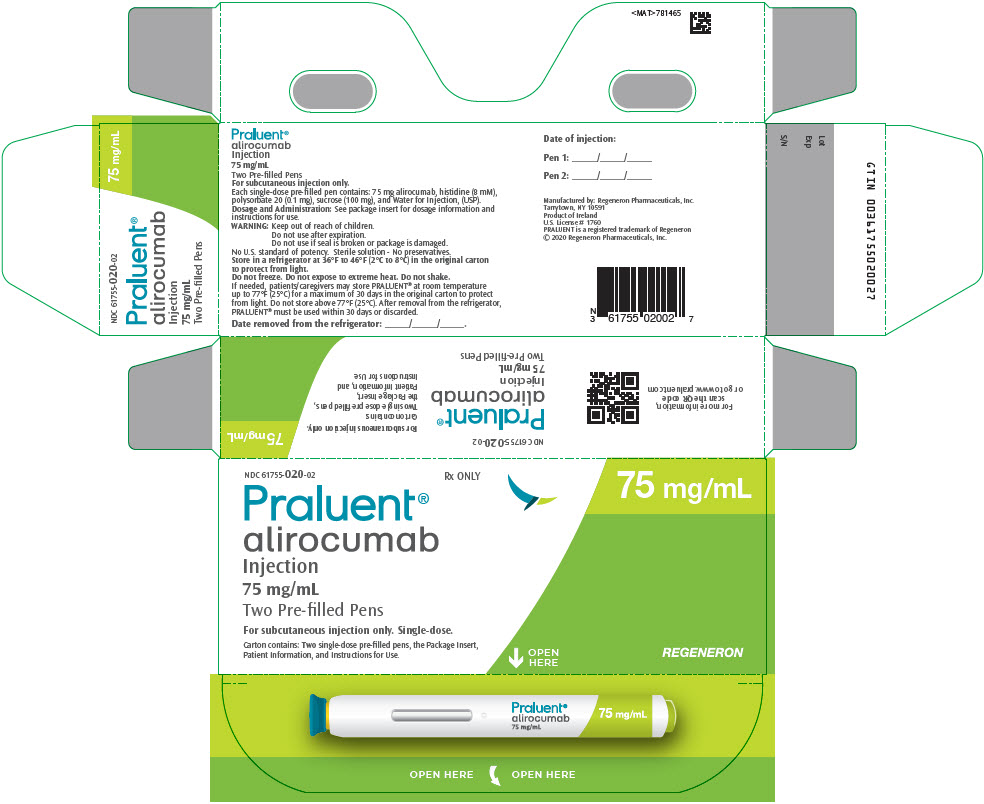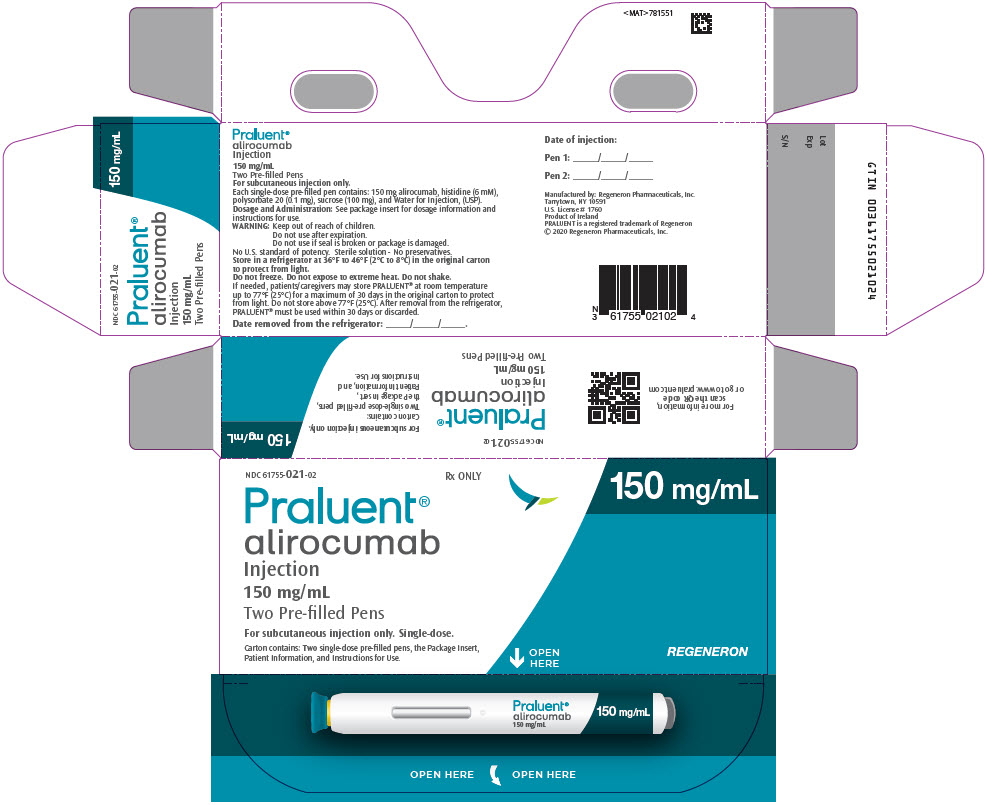 DRUG LABEL: Praluent
NDC: 61755-020 | Form: INJECTION, SOLUTION
Manufacturer: Regeneron Pharmaceuticals, Inc.
Category: prescription | Type: HUMAN PRESCRIPTION DRUG LABEL
Date: 20251030

ACTIVE INGREDIENTS: ALIROCUMAB 75 mg/1 mL
INACTIVE INGREDIENTS: HISTIDINE; POLYSORBATE 20; SUCROSE; WATER

HIGHLIGHTS OF PRESCRIBING INFORMATION

These highlights do not include all the information needed to use PRALUENT safely and effectively. See full prescribing information for PRALUENT.
PRALUENT® (alirocumab) injection, for subcutaneous use
Initial U.S. Approval: 2015

RECENT MAJOR CHANGES

Indications and Usage (1) | 10/2025

1 INDICATIONS AND USAGE

PRALUENT is a proprotein convertase subtilisin kexin type 9 (PCSK9) inhibitor indicated:

- To reduce the risk of major adverse cardiovascular (CV) events (coronary heart disease death, myocardial infarction, stroke, or unstable angina requiring hospitalization) in adults at increased risk for these events. (1)
- As an adjunct to diet and exercise to reduce low-density lipoprotein cholesterol (LDL-C) in :
  - adults with hypercholesterolemia (1)
  - adults and pediatric patients aged 8 years and older with heterozygous familial hypercholesterolemia (HeFH). (1)
  - adults with homozygous familial hypercholesterolemia (HoFH). (1)

2 DOSAGE AND ADMINISTRATION

- In adults with hypercholesterolemia, including HeFH (2.1):
  - The recommended starting dosage of PRALUENT is either 75 mg once every 2 weeks or 300 mg once every 4 weeks administered subcutaneously.
  - For patients receiving PRALUENT 300 mg every 4 weeks, measure LDL-C just prior to the next scheduled dosage, because LDL-C can vary between dosages in some patients.
  - If the LDL-C response is inadequate, the dosage may be adjusted 150 mg subcutaneously every 2 weeks.
- In adults with HeFH undergoing LDL apheresis or in adults with HoFH (2.1):
  - The recommended dosage of PRALUENT is 150 mg once every 2 weeks administered subcutaneously.
  - PRALUENT can be administered without regard to the timing of LDL apheresis.
- In pediatric patients with HeFH (2.2):
  - The recommended dosage of PRALUENT for patients with a body weight less than 50 kg is 150 mg once every 4 weeks administered subcutaneously.
  - The recommended dosage of PRALUENT for patients with a body weight of 50 kg or more is 300 mg once every 4 weeks administered subcutaneously.
  - If the LDL-C response is inadequate, the dosage may be adjusted for patients with a body weight less than 50 kg to 75 mg subcutaneously once every 2 weeks or for patients with a body weight of 50 kg or more to 150 mg subcutaneously once every 2 weeks.
- Assess LDL-C when clinically appropriate. The LDL-lowering effect of PRALUENT may be measured as early as 4 weeks after initiation. (2.1)
- Administer PRALUENT subcutaneously into areas of the thigh, abdomen, or upper arm that are not tender, bruised, red, or indurated. Rotate injection sites for each administration. (2.4)
- To administer the 300 mg dosage, give two 150 mg PRALUENT injections consecutively at two different injection sites. (2.4)

3 DOSAGE FORMS AND STRENGTHS

Injection: 75 mg/mL or 150 mg/mL in a single-dose pre-filled pen. (3)

4 CONTRAINDICATIONS

History of a serious hypersensitivity reaction to alirocumab or any of the excipients in PRALUENT. (4)

5 WARNINGS AND PRECAUTIONS

Hypersensitivity reactions: hypersensitivity vasculitis, angioedema, and other hypersensitivity reactions requiring hospitalization, have been reported with PRALUENT treatment. If signs or symptoms of serious hypersensitivity reactions occur, discontinue treatment with PRALUENT, treat according to the standard of care, and monitor until signs and symptoms resolve. (5.1)

6 ADVERSE REACTIONS

Common (>5% of patients treated with PRALUENT and more frequently than placebo) adverse reactions in adults with:

Primary hypercholesterolemia: injection site reactions, and influenza. (6) Established CV disease: myalgia. (6)

To report SUSPECTED ADVERSE REACTIONS, contact Regeneron at 1-844-734-6643 or FDA at 1-800-FDA-1088 or www.fda.gov/medwatch.

FULL PRESCRIBING INFORMATION

1 INDICATIONS AND USAGE

PRALUENT® is indicated:

- To reduce the risk of major adverse cardiovascular (CV) events (coronary heart disease death, myocardial infarction, stroke, or unstable angina requiring hospitalization) in adults at increased risk for these events.
- As an adjunct to diet and exercise to reduce low- density lipoprotein cholesterol (LDL-C) in:
  - adults with hypercholesterolemia.
  - adults and pediatric patients aged 8 years and older with heterozygous familial hypercholesterolemia (HeFH).
  - adults with homozygous familial hypercholesterolemia (HoFH).

2 DOSAGE AND ADMINISTRATION

2.1 Recommended Dosage in Adults

- Hypercholesterolemia, including HeFH:
  - The recommended starting dosage of PRALUENT is either 75 mg once every 2 weeks or 300 mg once every 4 weeks administered subcutaneously [see Dosage and Administration (2.4)].
  - For patients receiving PRALUENT 300 mg every 4 weeks, measure LDL-C just prior to the next scheduled dose, because LDL-C can vary between doses in some patients [see Clinical Studies (14)].
  - If the LDL-C response is inadequate, the dosage may be adjusted to 150 mg subcutaneously every 2 weeks.
- HeFH undergoing LDL apheresis or with HoFH:
  - The recommended dosage of PRALUENT is 150 mg once every 2 weeks administered subcutaneously [see Dosage and Administration (2.4)].
  - PRALUENT can be administered without regard to the timing of LDL apheresis.
- Assess LDL-C when clinically appropriate. The LDL-lowering effect of PRALUENT may be measured as early as 4 weeks after initiation.

2.2 Recommended Dosage in Pediatric Patients Aged 8 years and Older With HeFH

- The recommended dosage of PRALUENT for patients with a body weight less than 50 kg is 150 mg once every 4 weeks administered subcutaneously [see Dosage and Administration (2.4)].
  - If the LDL-C lowering response is inadequate, the dosage may be adjusted to 75 mg subcutaneously once every 2 weeks [see Dosage and Administration (2.4)].
- The recommended dosage of PRALUENT for patients with a body weight of 50 kg or more is 300 mg once every 4 weeks administered subcutaneously [see Dosage and Administration (2.4)].
  - If the LDL-C lowering response is inadequate, the dosage may be adjusted to 150 mg subcutaneously once every 2 weeks [see Dosage and Administration (2.4)].
- Assess LDL-C when clinically appropriate. The LDL-lowering effect of PRALUENT may be measured as early as 4 weeks after initiation.

2.3 Missed Doses

If a dose is missed:

- Within 7 days from the missed dose, instruct the patient to administer PRALUENT and resume the patient's original schedule.
- More than 7 days after the missed dose:
  - For every 2-week dosage, instruct the patient to wait until the next dose on the original schedule.
  - For every 4-week dosage, instruct the patient to administer the dose and start a new schedule based on this date.

2.4 Important Administration Instructions

- Train patients and/or caregivers on how to prepare and administer PRALUENT, according to the Instructions for Use and instruct them to read and follow the Instructions for Use each time they use PRALUENT.
- In children aged 12 to 17 years, it is recommended that PRALUENT be given by or under the supervision of an adult. In children aged 8 to 11 years, PRALUENT should be given by a caregiver.
- Prior to use, allow PRALUENT to warm to room temperature for 30 to 40 minutes if PRALUENT has been refrigerated [see How Supplied/Storage and Handling (16)].
- Visually inspect PRALUENT prior to administration. PRALUENT is a clear, colorless to pale yellow solution. Do not use if the solution is cloudy, discolored, or contains particles.
- Administer PRALUENT subcutaneously into areas of the thigh, abdomen, or upper arm that are not tender, bruised, red, or indurated. Rotate injection sites for each administration. It may take up to 20 seconds to inject PRALUENT.
- To administer the 300 mg dose, give two 150 mg PRALUENT injections consecutively at two different injection sites.

3 DOSAGE FORMS AND STRENGTHS

PRALUENT injection is a clear, colorless to pale yellow solution available as follows:

- 75 mg/mL single-dose pre-filled pen
- 150 mg/mL single-dose pre-filled pen

4 CONTRAINDICATIONS

PRALUENT is contraindicated in patients with a history of a serious hypersensitivity reaction to alirocumab or any of the excipients in PRALUENT. Hypersensitivity vasculitis, angioedema, and hypersensitivity reactions requiring hospitalization have occurred [see Warnings and Precautions (5.1)].

5 WARNINGS AND PRECAUTIONS

5.1 Hypersensitivity Reactions

Hypersensitivity reactions, including hypersensitivity vasculitis, angioedema, and other hypersensitivity reactions requiring hospitalization, have been reported with PRALUENT treatment. If signs or symptoms of serious hypersensitivity reactions occur, discontinue treatment with PRALUENT, treat according to the standard of care, and monitor until signs and symptoms resolve. PRALUENT is contraindicated in patients with a history of a serious hypersensitivity reaction to alirocumab or any excipient in PRALUENT [see Contraindications (4)].

6 ADVERSE REACTIONS

The following adverse reactions are also discussed in the other sections of the labeling:

- Hypersensitivity Reactions [see Warnings and Precautions (5.1)]

6.1 Clinical Trials Experience

Because clinical trials are conducted under widely varying conditions, adverse reaction rates observed in the clinical trials of a drug cannot be directly compared to rates in the clinical trials of another drug and may not reflect the rates observed in practice.

Adverse Reactions in Adults with Hypercholesterolemia

The data in Table 1 are derived from 9 primary hypercholesterolemia placebo-controlled trials that included 2,476 adult patients treated with PRALUENT 75 mg and/or 150 mg every 2 weeks, including 2,135 exposed for 6 months and 1,999 exposed for more than 1 year (median treatment duration of 65 weeks). The mean age of the population was 59 years, 40% of the population were female, 90% were White, 4% were Black or African American, 3% were Asian, and 3% other races; 6% identified as Hispanic or Latino ethnicity.

Adverse reactions reported in at least 2% of PRALUENT-treated patients, and more frequently than in placebo-treated patients, are shown in Table 1.

Table 1: Adverse Reactions Occurring in >2% of PRALUENT-Treated Adult Patients and ≥1% More Frequently Than with Placebo
Adverse Reactions | Placebo (N=1,276) % | PRALUENT [75 mg every 2 weeks and 150 mg every 2 weeks combined] (N=2,476) %
Injection site reactions [Includes erythema/redness, itching, swelling, pain/tenderness] | 5 | 7
Influenza | 5 | 6
Diarrhea | 4 | 5
Myalgia | 3 | 4
Muscle spasms | 2 | 3
Contusion | 1 | 2

Adverse reactions led to discontinuation of treatment in 5.3% of patients treated with PRALUENT and 5.1% of patients treated with placebo. The most common adverse reactions leading to treatment discontinuation in patients treated with PRALUENT were allergic reactions (0.6% versus 0.2% for PRALUENT and placebo, respectively) and elevated liver enzymes (0.3% versus <0.1%).

In an analysis of ezetimibe-controlled trials in which 864 patients were exposed to PRALUENT for a median of 27 weeks and 618 patients were exposed to ezetimibe for a median of 24 weeks, the types and frequencies of common adverse reactions were similar to those listed above.

Adverse Reactions in a Cardiovascular Outcomes Trial in Adults

In a CV outcomes trial in which 9,451 patients were exposed to PRALUENT for a median of 31 months and 9,443 patients were exposed to placebo for a median of 32 months, common adverse reactions (greater than 5% of patients treated with PRALUENT and occurring more frequently than placebo) included myalgia (6% PRALUENT, 5% placebo).

Adverse Reactions in Pediatric Patients with HeFH

In a 24-week placebo-controlled clinical trial in which 101 pediatric patients aged 8 to 17 years with HeFH were exposed to PRALUENT and 52 pediatric patients with HeFH were exposed to placebo [see Clinical Studies (14.3)], the safety profile of PRALUENT observed in this population was consistent with the safety profile observed in adults with HeFH.

Other Adverse Reactions

Local Injection Site Reactions

In a pool of placebo-controlled trials evaluating PRALUENT 75 mg and/or 150 mg administered every 2 weeks in adults, local injection site reactions including erythema/redness, itching, swelling, and pain/tenderness were reported more frequently in patients treated with PRALUENT (7.2% versus 5.1% for PRALUENT and placebo, respectively). Few patients discontinued treatment because of these reactions (0.2% versus 0.4% for PRALUENT and placebo, respectively), but patients receiving PRALUENT had a greater number of injection site reactions, had more reports of associated symptoms, and had reactions of longer average duration than patients receiving placebo.

In a 48-week placebo-controlled trial evaluating PRALUENT 300 mg every 4 weeks and 75 mg every 2 weeks in adults, in which all patients received an injection of drug or placebo every 2 weeks, local injection site reactions were reported more frequently in patients treated with PRALUENT 300 mg every 4 weeks as compared to those receiving PRALUENT 75 mg every 2 weeks or placebo (16.6%, 9.6%, and 7.9%, respectively). Three patients (0.7%) treated with PRALUENT 300 mg every 4 weeks discontinued treatment due to local injection site reactions versus no patients (0%) in the other 2 treatment groups.

In a CV outcomes trial in adults, local injection site reactions were reported in 3.8% of patients treated with PRALUENT versus 2.1% patients treated with placebo, and led to permanent discontinuation in 26 patients (0.3%) versus 3 patients (<0.1%), respectively.

In the trial of pediatric patients with HeFH, local injection site reactions were reported in 5% of patients treated with PRALUENT versus 0% patients treated with placebo; no patients discontinued treatment due to injection site reactions.

Hypersensitivity Reactions in Adults

Hypersensitivity reactions were reported more frequently in adult patients treated with PRALUENT than in those treated with placebo (8.6% versus 7.8%). The most common hypersensitivity reaction was pruritus (1.1% versus 0.4% for PRALUENT and placebo, respectively). The proportion of patients who discontinued treatment due to allergic reactions was higher among those treated with PRALUENT (0.6% versus 0.2%).

Serious allergic reactions, such as hypersensitivity, nummular eczema, and hypersensitivity vasculitis were reported in patients using PRALUENT in controlled clinical trials.

Liver Enzyme Abnormalities in Adults

In the hypercholesterolemia trials in adults, liver-related disorders (primarily related to abnormalities in liver enzymes) were reported in 2.5% of patients treated with PRALUENT and 1.8% of patients treated with placebo, leading to treatment discontinuation in 0.4% and 0.2% of patients, respectively. Increases in serum transaminases to greater than 3 times the upper limit of normal occurred in 1.7% of patients treated with PRALUENT and 1.4% of patients treated with placebo.

6.2 Postmarketing Experience

The following adverse reactions have been reported during post-approval use of PRALUENT. Because these reactions are reported voluntarily from a population of uncertain size, it is not always possible to reliably estimate their frequency or establish a causal relationship to drug exposure.

- Hypersensitivity reactions: Angioedema
- Influenza-like illness

8 USE IN SPECIFIC POPULATIONS

8.1 Pregnancy

Risk Summary

Available data from clinical trials and postmarketing reports on PRALUENT use in pregnant women are insufficient to evaluate for a drug-associated risk of major birth defects, miscarriage or other adverse maternal or fetal outcomes. In animal reproduction studies, there were no effects on embryo-fetal development when rats were subcutaneously administered alirocumab during organogenesis at dose exposures up to 12-fold the exposure at the maximum recommended human dose of 150 mg every two weeks. In monkeys, suppression of the humoral immune response was observed in infant monkeys when alirocumab was dosed during organogenesis to parturition at dose exposures 13-fold the exposure at the maximum recommended human dose of 150 mg every two weeks. No additional effects on pregnancy or neonatal/infant development were observed at dose exposures up to 81-fold the maximum recommended human dose of 150 mg every two weeks. Measurable alirocumab serum concentrations were observed in the infant monkeys at birth at comparable levels to maternal serum, indicating that alirocumab, like other IgG antibodies, crosses the placental barrier. Monoclonal antibodies are transported across the placenta in increasing amounts especially near term; therefore, alirocumab has the potential to be transmitted from the mother to the developing fetus.

The estimated background risk of major birth defects and miscarriage for the indicated population(s) is unknown. In the U.S. general population, the estimated background risk of major birth defects and miscarriage in clinically recognized pregnancies is 2%-4% and 15%-20%, respectively.

There is a pregnancy safety study for PRALUENT. If PRALUENT is administered during pregnancy, healthcare providers should report PRALUENT exposure by contacting Regeneron at 1-844-734-6643.

Data

Animal data

In Sprague Dawley rats, no effects on embryo-fetal development were observed when alirocumab was dosed at up to 75 mg/kg/dose by the subcutaneous route on gestation days 6 and 12 at exposures 12-fold the maximum recommended human dose of 150 mg every two weeks, based on serum AUC.

In cynomolgus monkeys, suppression of the humoral immune response to keyhole limpet hemocyanin (KLH) antigen was observed in infant monkeys at 4 to 6 months of age when alirocumab was dosed during organogenesis to parturition at 15 mg/kg/week and 75 mg/kg/week by the subcutaneous route, corresponding to 13-fold and 81-fold the human exposure at the maximum recommended human dose of 150 mg every two weeks, based on serum AUC. The lowest dose tested in the monkey resulted in humoral immune suppression; therefore, it is unknown if this effect would be observed at clinical exposure. No study designed to challenge the immune system of infant monkeys was conducted. No additional embryo-fetal, prenatal or postnatal effects were observed in infant monkeys, and no maternal effects were observed, when alirocumab was dosed at up to 75 mg/kg/week by the subcutaneous route, corresponding to maternal exposure of 81-fold the exposure at the maximum recommended human dose of 150 mg every two weeks, based on serum AUC.

8.2 Lactation

Risk Summary

There is no information regarding the presence of alirocumab in human milk, the effects on the breastfed infant, or the effects on milk production. The development and health benefits of breastfeeding should be considered along with the mother's clinical need for PRALUENT and any potential adverse effects on the breastfed infant from PRALUENT or from the underlying maternal condition. Human IgG is present in human milk, but published data suggest that breast milk IgG antibodies do not enter the neonatal and infant circulation in substantial amounts.

8.4 Pediatric Use

The safety and effectiveness of PRALUENT as an adjunct to diet and other LDL-C-lowering therapies for the treatment of HeFH have been established in pediatric patients aged 8 years and older. Use of PRALUENT for this indication is based on data from a 24-week, randomized, placebo-controlled, double-blind trial in pediatric patients with HeFH. In the trial, 101 patients received PRALUENT and 52 patients received placebo; 26 patients (17%) were 8 to 9 years of age. This indication is supported by evidence from controlled trials in adults [see Adverse Reactions (6.1) and Clinical Studies (14.3)].

The safety and effectiveness of PRALUENT have not been established in pediatric patients with HeFH who are younger than 8 years of age or in pediatric patients with other types of hypercholesterolemia.

8.5 Geriatric Use

In controlled trials, 3663 patients treated with PRALUENT were ≥65 years of age and 734 patients treated with PRALUENT were ≥75 years of age. No overall differences in safety or effectiveness were observed between these patients and younger patients, and other reported clinical experience has not identified differences in responses between the elderly and younger patients, but greater sensitivity of some older individuals cannot be ruled out.

8.6 Renal Impairment

No dose adjustment is needed for patients with mild or moderately impaired renal function. No data are available in patients with severe renal impairment [see Clinical Pharmacology (12.3)].

8.7 Hepatic Impairment

No dose adjustment is needed for patients with mild or moderate hepatic impairment. No data are available in patients with severe hepatic impairment [see Clinical Pharmacology (12.3)].

11 DESCRIPTION

Alirocumab is a human monoclonal antibody (IgG1 isotype) that targets proprotein convertase subtilisin kexin type 9 (PCSK9). Alirocumab is a PCSK9 inhibitor produced by recombinant DNA technology in Chinese Hamster Ovary cell suspension culture. Alirocumab consists of two disulfide-linked human heavy chains, each covalently linked through a disulfide bond to a human kappa light chain. A single N-linked glycosylation site is located in each heavy chain within the CH2 domain of the Fc constant region of the molecule. The variable domains of the heavy and light chains combine to form the PCSK9 binding site within the antibody. Alirocumab has an approximate molecular weight of 146 kDa.

PRALUENT is a sterile, preservative-free, clear, colorless to pale yellow solution for subcutaneous use. PRALUENT 75 mg/mL or 150 mg/mL solution for subcutaneous injection in a single-dose pre-filled pen is supplied in a siliconized 1 mL Type-1 clear glass syringe.

Each 75 mg/mL pre-filled pen contains 75 mg alirocumab, histidine (8 mM), polysorbate 20 (0.1 mg), sucrose (100 mg), and Water for Injection USP, to pH 6.0.

Each 150 mg/mL pre-filled pen contains 150 mg alirocumab, histidine (6 mM), polysorbate 20 (0.1 mg), sucrose (100 mg), and Water for Injection USP, to pH 6.0.

12 CLINICAL PHARMACOLOGY

12.1 Mechanism of Action

Alirocumab is a human monoclonal antibody that binds to proprotein convertase subtilisin kexin type 9 (PCSK9). PCSK9 binds to the low-density lipoprotein (LDL) receptors (LDLR) on the surface of hepatocytes to promote LDLR degradation within the liver. By inhibiting the binding of PCSK9 to LDLR, alirocumab increases the number of LDLRs available to clear LDL, thereby lowering LDL-C levels.

12.2 Pharmacodynamics

Alirocumab reduced free PCSK9 in a concentration-dependent manner. Following a single subcutaneous administration of alirocumab 75 or 150 mg, maximal suppression of free PCSK9 occurred within 4 to 8 hours. Free PCSK9 concentrations returned to baseline when alirocumab concentrations decreased below the limit of quantitation.

12.3 Pharmacokinetics

Absorption

After subcutaneous administration of 75 mg to 300 mg alirocumab, median times to maximum serum concentrations (tmax) were 3-7 days. The pharmacokinetics of alirocumab after single subcutaneous administration of 75 mg into the abdomen, upper arm, or thigh were similar. The absolute bioavailability of alirocumab after subcutaneous administration was about 85% as determined by population pharmacokinetics analysis. A slightly greater than dose proportional increase was observed, with a 2.1-fold to 2.7-fold increase in total alirocumab concentrations for a 2-fold increase in dose from 75 mg every 2 weeks to 150 mg every 2 weeks. Monthly dose normalized exposure with 300 mg every 4 weeks treatment was similar to that of 150 mg every 2 weeks. Steady state was reached after 2 to 3 doses with an accumulation ratio up to a maximum of about 2-fold.

Distribution

Following intravenous administration, the volume of distribution was about 0.04 to 0.05 L/kg indicating that alirocumab is distributed primarily in the circulatory system.

Elimination

Specific metabolism studies were not conducted, because alirocumab is a protein. Alirocumab is expected to degrade to small peptides and individual amino acids. In clinical studies where alirocumab was administered in combination with atorvastatin or rosuvastatin, no relevant changes in statin concentrations were observed in the presence of repeated administration of alirocumab, indicating that cytochrome P450 enzymes (mainly CYP3A4 and CYP2C9) and transporter proteins such as P-gp and OATP were not affected by alirocumab.

Two elimination phases were observed for alirocumab. At low concentrations, the elimination is predominately through saturable binding to target (PCSK9), while at higher concentrations the elimination of alirocumab is largely through a non-saturable proteolytic pathway.

Based on a population pharmacokinetic analysis, the median apparent half-life of alirocumab at steady state was 17 to 20 days in patients receiving alirocumab at subcutaneous doses of 75 mg every 2 weeks or 150 mg every 2 weeks.

Specific Populations

A population pharmacokinetic analysis was conducted on data from 2799 patients. Age, body weight, gender, race, and creatinine clearance were found not to significantly influence alirocumab pharmacokinetics.

Pediatric Patients

The pharmacokinetics of alirocumab were evaluated in 140 pediatric patients aged 8 to 17 years with HeFH. Steady-state concentrations were reached at or before week 8 (first PK sampling during repeated dosing) with recommended dosing regimen [see Dosage and Administration (2.2)].

Renal Impairment

Since monoclonal antibodies are not known to be eliminated via renal pathways, renal function is not expected to impact the pharmacokinetics of alirocumab.

No data are available in patients with severe renal impairment.

Hepatic Impairment

Following administration of a single 75 mg SC dose, alirocumab pharmacokinetic profiles in patients with mild and moderate hepatic impairment were similar to those in patients with normal hepatic function.

No data are available in patients with severe hepatic impairment.

Drug-Drug Interactions

The median apparent half-life of alirocumab is reduced to 12 days when administered with a statin; however, this difference is not clinically meaningful.

12.6 Immunogenicity

The observed incidence of anti-drug antibodies is highly dependent on the sensitivity and specificity of the assay. Differences in assay methods preclude meaningful comparisons of the incidence of anti-drug antibodies in the trials described below with the incidence of anti-drug antibodies in other trials, including those of PRALUENT or of other alirocumab products.

In adult patients with CV disease (Trial 1), the incidence of anti-alirocumab antibody (ADA) formation was 5.5% (504/9,091) in patients treated with PRALUENT 75 mg and/or 150 mg every 2 weeks for up to 5 years (with a median treatment exposure of 31 months). Neutralizing antibody (NAb) responses were observed in 0.5% (43/9,091) of all patients treated with PRALUENT. Of the patients who developed ADA, 8.5% (43/504) tested positive for NAb.

- While reductions in LDL-C were generally comparable in patients with or without ADA, including NAbs, some adult patients treated with PRALUENT with persistent or neutralizing antibodies experienced attenuation in LDL-C efficacy.
- Adult patients who developed ADA had a higher incidence of injection site reactions compared to patients without ADA (7.5% vs 3.6%) [see Adverse Reactions (6.1)].

In a pool of placebo-controlled and active-controlled trials of adult patients treated with PRALUENT 75 mg and/or 150 mg every 2 weeks as well as in a separate clinical trial of patients treated with PRALUENT 75 mg every 2 weeks or 300 mg every 4 weeks (including some patients with dose adjustment to 150 mg every 2 weeks), during the treatment period ranging from 6 to 24 months, the incidence of detecting ADA was 4.8% (147/3033) and NAb was 1.2% (36/3,033), which was similar to the results from the trial described above.

In pediatric patients aged 8 to 17 years with HeFH (Trial 12), the incidence of ADA for patients treated with PRALUENT was 3% (3/98) with a median treatment exposure of 24 weeks in patients receiving PRALUENT once every 2 weeks and 23 weeks in patients receiving PRALUENT once every 4 weeks with an optional up-titration. Of the 3 pediatric patients who developed ADA, no one tested positive for NAb.

Because of the low occurrence of ADA and the small number of pediatric patients enrolled, the effect of these antibodies on the pharmacokinetics, pharmacodynamics, safety, and/or effectiveness of PRALUENT in pediatric patients is unknown.

13 NONCLINICAL TOXICOLOGY

13.1 Carcinogenesis, Mutagenesis, Impairment of Fertility

Carcinogenicity studies have not been conducted with alirocumab. The mutagenic potential of alirocumab has not been evaluated; however, monoclonal antibodies are not expected to alter DNA or chromosomes.

There were no adverse effects on surrogate markers of fertility (e.g., estrous cyclicity, testicular volume, ejaculate volume, sperm motility, or total sperm count per ejaculate) in a 6-month chronic toxicology study in sexually-mature monkeys subcutaneously administered at 5, 15, and 75 mg/kg/week at systemic exposures up to 103-fold the 150 mg every two weeks subcutaneous clinical dose based on serum AUC. In addition, there were no adverse alirocumab-related anatomic pathology or histopathology findings in reproductive tissues in rat or monkey toxicology studies at systemic exposures up to 11-fold and 103-fold respectively, in the 6-month studies, compared to clinical systemic exposure following a 150 mg every two weeks dose, based on serum AUC.

13.2 Animal Toxicology and/or Pharmacology

During a 13-week toxicology study of 75 mg/kg once weekly alirocumab in combination with 40 mg/kg once daily atorvastatin in adult monkeys, there were no effects of PRALUENT on the humoral immune response to keyhole limpet hemocyanin (KLH) after one to two months at exposures 100-fold greater than the exposure at the maximum recommended human dose of 150 mg every two weeks, based on AUC.

14 CLINICAL STUDIES

14.1 Cardiovascular Outcome Trial in Adult Patients with Established Cardiovascular Disease

Trial 1 (ODYSSEY OUTCOMES, NTC01663402) was a multicenter, double-blind, placebo-controlled trial in 18,924 adult patients (9,462 PRALUENT; 9,462 placebo) followed for up to 5 years. Patients had an acute coronary syndrome (ACS) event 4 to 52 weeks prior to randomization and were treated with a lipid-modifying therapy (LMT) regimen that was statin-intensive (defined as atorvastatin 40 or 80 mg, or rosuvastatin 20 or 40 mg) or at maximally tolerated dose of a statin, with or without other LMT. Patients were randomized to receive either PRALUENT 75 mg or placebo once every two weeks.

At month 2, if additional LDL-C lowering was required based on pre-specified LDL-C criteria (LDL-C ≥50 mg/dL), PRALUENT was adjusted to 150 mg every 2 weeks. For patients who had their dose adjusted to 150 mg every 2 weeks and who had two consecutive LDL-C values below 25 mg/dL, down-titration from 150 mg every 2 weeks to 75 mg every 2 weeks was performed. Patients on 75 mg every 2 weeks who had two consecutive LDL-C values below 15 mg/dL were switched to placebo in a blinded fashion. Approximately 2615 (27.7%) of 9,451 patients treated with PRALUENT required dose adjustment to 150 mg every 2 weeks. Of these 2,615 patients, 805 (30.8%) were down-titrated to 75 mg every 2 weeks. Overall, 730 (7.7%) of 9,451 patients switched to placebo.

A total of 99.5% of patients were followed for survival until the end of the trial. The median follow-up duration was 33 months.

Baseline Disease and Demographic Characteristics

The mean age at baseline was 59 years (range 39-92), with 25% female, and 27% at least 65 years old. The trial population was 79% White, 3% Black or African American and 13% Asian; 17% identified as Hispanic or Latino ethnicity. The index ACS event was a myocardial infarction in 83% of patients and unstable angina in 17% of patients. Prior to the index ACS event, 19% had prior myocardial infarction and 23% had coronary revascularization procedures (CABG/PCI). Selected additional baseline risk factors included hypertension (65%), diabetes mellitus (25%), New York Heart Association class I or II congestive heart failure (15%), and eGFR <60 mL/min/1.73 m^2 (13%). Most patients (89%) were receiving statin-intensive therapy with or without other LMT at randomization. The mean LDL-C value at baseline was 92.4 mg/dL.

Endpoint Results

PRALUENT significantly reduced the risk for the primary composite endpoint (time to first occurrence of coronary heart disease death, non-fatal myocardial infarction, fatal and non-fatal ischemic stroke, or unstable angina requiring hospitalization: p=0.0003). The results are presented in Table 2.

Table 2: Cardiovascular Outcomes in Adult Patients with Established Cardiovascular Disease
Endpoint | PRALUENT N=9,462 |  | Placebo N=9,462 |  | Hazard Ratio (95% CI) [Cox-proportional hazards model with treatment as a factor and stratified by geographic region]
Endpoint | n (%) | Incidence Rate per 100 Patient Years (95% CI) | n (%) | Incidence Rate per 100 Patient Years (95% CI) | Hazard Ratio (95% CI) [Cox-proportional hazards model with treatment as a factor and stratified by geographic region]
Primary composite endpoint [Primary composite endpoint defined as: time to first occurrence of coronary heart disease death, non-fatal myocardial infarction, fatal and non-fatal ischemic stroke, or unstable angina requiring hospitalization] | 903 (9.5%) | 3.5 (3.3 to 3.8) | 1052 (11.1%) | 4.2 (3.9 to 4.4) | 0.85 (0.78, 0.93)
Components of the Primary Composite Endpoint [First occurrence of specified event at any time; patients may have experienced more than one adjudicated event]
CHD death | 205 (2.2%) | 0.8 (0.7 to 0.9) | 222 (2.3%) | 0.8 (0.7 to 0.9) | 0.92 (0.76, 1.11)
Non-fatal MI [Statistical testing performed outside hierarchy; therefore not considered statistically significant] | 626 (6.6%) | 2.4 (2.2 to 2.6) | 722 (7.6%) | 2.8 (2.6 to 3.0) | 0.86 (0.77, 0.96)
Fatal or non-fatal ischemic stroke | 111 (1.2%) | 0.4 (0.3 to 0.5) | 152 (1.6%) | 0.6 (0.5 to 0.7) | 0.73 (0.57, 0.93)
Unstable angina requiring hospitalization | 37 (0.4%) | 0.1 (0.1 to 0.2) | 60 (0.6%) | 0.2 (0.2 to 0.3) | 0.61 (0.41, 0.92)
Mortality Endpoint (not statistically significant per pre-specified method to control for type I error)
All-cause mortality | 334 (3.5%) | 1.2 (1.1 to 1.4) | 392 (4.1%) | 1.5 (1.3 to 1.6) | 0.85 (0.73, 0.98)

The Kaplan-Meier estimates of the cumulative incidence of the primary endpoint over time is presented in Figure 1.

Figure 1: Primary Composite Endpoint Cumulative Incidence over 4 Years in ODYSSEY OUTCOMES

14.2 Clinical Trials in Adult Patients with Primary Hypercholesterolemia (including HeFH) and HoFH

Primary Hypercholesterolemia

Trial 2 (ODYSSEY LONG TERM, NCT01507831) was a multicenter, double-blind, placebo-controlled trial that randomly assigned 1,553 adult patients to PRALUENT 150 mg every 2 weeks and 788 adult patients to placebo. All patients were taking maximally tolerated doses of statins with or without other lipid-modifying therapy and required additional LDL-C reduction.

Baseline Disease and Demographic Characteristics

The mean age was 61 years (range 18-89), 38% were female, 93% were White, 3% were Black or African American, and 5% identified as Hispanic or Latino ethnicity. The average LDL-C at baseline was 122 mg/dL.

Endpoint Results

At week 24, the treatment difference between PRALUENT and placebo in mean LDL-C percent change was -58% (95% CI: -61%, -56%; p-value: ˂0.0001).

The proportion of patients who prematurely discontinued trial drug prior to the 24-week primary endpoint was 8% among those treated with PRALUENT and 8% among those treated with placebo.

For additional results see Table 3 and Figure 2.

Table 3: Mean Percent Change from Baseline and Difference [Difference is PRALUENT minus Placebo] from Placebo in Lipid Parameters at Week 24 in ODYSSEY LONG TERM [A pattern-mixture model approach was used with multiple imputation of missing post-treatment values based on a patient's own baseline value and multiple imputation of missing on-treatment values based on a model including available on-treatment values]
Treatment Group | LDL-C | Total-C | Non-HDL-C | Apo B
Week 24 (Mean Percent Change from Baseline)
Placebo (n=788) | 1 | 0 | 1 | 1
PRALUENT 150 mg (n=1,553) | -58 | -36 | -49 | -50
Difference from placebo (LS Mean) (95% CI) | -58 (-61, -56) | -36 (-37, -34) | -50 (-52, -47) | -51 (-53, -48)

Figure 2: Mean Percent Change from Baseline in LDL-C Over 52 Weeks in Adult Patients on Maximally Tolerated Statin Treated with PRALUENT 150 mg Every 2 Weeks and Placebo Every 2 Weeks (ODYSSEY LONG TERM)a

a The means were estimated based on all randomized patients, with multiple imputation of missing data taking into account treatment adherence

b Number of patients with observed data

Trial 3 (ODYSSEY COMBO I, NCT01644175) was a multicenter, double-blind, placebo-controlled trial that randomly assigned 209 adult patients to PRALUENT and 107 adult patients to placebo. Patients were taking maximally tolerated doses of statins with or without other lipid-modifying therapy and required additional LDL-C reduction.

Baseline Disease and Demographic Characteristics

The mean age was 63 years (range 39-87), 34% were female, 82% were White, 16% were Black or African American, and 11% were Hispanic or Latino. Mean baseline LDL-C was 102 mg/dL.

Endpoint Results

At week 12, the mean percent change from baseline in LDL-C was -45% with PRALUENT compared to 1% with placebo, and the treatment difference between PRALUENT 75 mg every 2 weeks and placebo in mean LDL-C percent change was -46% (95% CI: -53%, -39%).

At week 12, if additional LDL-C lowering was required based on pre-specified LDL-C criteria, PRALUENT was up-titrated to 150 mg every 2 weeks for the remainder of the trial. The dose was up-titrated to 150 mg every 2 weeks in 32 (17%) of 191 patients treated with PRALUENT for at least 12 weeks. At week 24, the mean percent change from baseline in LDL-C was -44% with PRALUENT and -2% with placebo, and the treatment difference between PRALUENT and placebo in mean LDL-C percent change was -43% (95% CI: -50%, -35%; p-value: ˂0.0001).

The proportion of patients who prematurely discontinued trial drug prior to the 24-week primary endpoint was 11% among those treated with PRALUENT and 12% among those treated with placebo.

Trials 4 (ODYSSEY FH I, NCT01623115) and 5 (ODYSSEY FH II, NCT01709500) were multicenter, double-blind, placebo-controlled trials that, combined, randomly assigned 490 adult patients to PRALUENT and 245 adult patients to placebo. The trials were similar with regard to both design and eligibility criteria. All patients had HeFH, were taking a maximally tolerated dose of statin with or without other lipid-modifying therapy, and required additional LDL-C reduction. The diagnosis of HeFH was made either by genotyping or clinical criteria ("definite FH" using either the Simon Broome or WHO/Dutch Lipid Network criteria).

Baseline Disease and Demographic Characteristics

The mean age was 52 years (range 20-87), 45% were female, 94% were White, 1% were Black or African American, and 3% identified as Hispanic or Latino ethnicity. The average LDL-C at baseline was 141 mg/dL.

Endpoint Results

At week 12, the treatment difference between PRALUENT 75 mg every 2 weeks and placebo in mean LDL-C percent change was -48% (95% CI: -52%, -44%).

At week 12, if additional LDL-C lowering was required based on pre-specified LDL-C criteria, PRALUENT was up-titrated to 150 mg every 2 weeks for the remainder of the trials. The dose was up-titrated to 150 mg every 2 weeks in 196 (42%) of 469 patients treated with PRALUENT for at least 12 weeks. At week 24, the mean treatment difference between PRALUENT and placebo in mean LDL-C percent change from baseline was -54% (95% CI: -59%, -50%; p-value: ˂0.0001). The LDL-C-lowering effect was sustained to week 52.

Considering both trials together, the proportion of patients who prematurely discontinued trial drug prior to the 24-week primary endpoint was 6% among those treated with PRALUENT and 4% among those treated with placebo.

For additional results see Table 4 and Figure 3.

Table 4: Mean Percent Change from Baseline and Difference [Difference is PRALUENT minus Placebo] from Placebo in Lipid Parameters at Week 12 and Week 24 in Adult Patients with HeFH (ODYSSEY FH I and FH II Pooled) [A pattern-mixture model approach was used with multiple imputation of missing post-treatment values based on a patient's own baseline value and multiple imputation of missing on-treatment values based on a model including available on-treatment values]
Treatment Group | LDL-C | Total-C | Non-HDL-C | Apo B
Week 12 (Mean Percent Change from Baseline)
Placebo (n=245) | 5 | 4 | 5 | 2
PRALUENT 75 mg (n=490) | -43 | -27 | -38 | -34
Difference from placebo (LS Mean) (95% CI) | -48 (-52, -44) | -31 (-34, -28) | -42 (-46, -39) | -36 (-39, -33)
Week 24 (Mean Percent Change from Baseline)
Placebo (n=245) | 7 | 5 | 7 | 2
PRALUENT 75 mg/150 mg [Dose was up-titrated to 150 mg every 2 weeks in 196 (42%) patients treated for at least 12 weeks] (n=490) | -47 | -30 | -42 | -40
Difference from placebo (LS Mean) (95% CI) | -54 (-59, -50) | -36 (-39, -33) | -49 (-53, -45) | -42 (-45, -39)

Figure 3: Mean Percent Change from Baseline in LDL-C Over 52 Weeks in Adult Patients with HeFH on Maximally Tolerated Statin Treated with PRALUENT 75/150 mg Every 2 Weeks and Placebo every 2 weeks (ODYSSEY FH I and FH II Pooled)a

a The means were estimated based on all randomized patients, with multiple imputation of missing data taking into account treatment adherence

b Number of patients with observed data

Trial 6 (ODYSSEY HIGH FH, NCT01617655) was a multicenter, double-blind, placebo-controlled trial that randomly assigned 72 adult patients to PRALUENT 150 mg every 2 weeks and 35 adult patients to placebo. Patients had HeFH with a baseline LDL-C ≥160 mg/dL while taking a maximally tolerated dose of statin with or without other lipid-modifying therapy.

Baseline Disease and Demographic Characteristics

The mean age was 51 years (range 18-80), 47% were female, 88% were White, 2% were Black or African American, and 6% identified as Hispanic or Latino ethnicity. The average LDL-C at baseline was 198 mg/dL.

Endpoint Results

At week 24, the mean percent change from baseline in LDL-C was -43% with PRALUENT and -7% with placebo, and the treatment difference between PRALUENT and placebo in mean LDL-C percent change was -36% (95% CI: -49%, -24%; p-value: <0.0001).

The proportion of patients who discontinued trial drug prior to the 24-week primary endpoint was 10% among those treated with PRALUENT and 0% among those treated with placebo.

Trial 7 (ODYSSEY CHOICE I, NCT01926782) was a multicenter, double-blind, placebo-controlled trial that randomly assigned 458 adult patients with hypercholesterolemia to PRALUENT 300 mg every 4 weeks, 115 adult patients to PRALUENT 75 mg every 2 weeks, and 230 adult patients to placebo. Patients were stratified based on whether or not they were treated concomitantly with statin.

Baseline Disease and Demographic Characteristics

The mean age was 61 years (range 21-88), 42% were female, 87% were White, 11% were Black or African American, and 3% identified as Hispanic or Latino ethnicity.

Endpoint Results

In the cohort of patients on background statin, the mean LDL-C at baseline was 113 mg/dL. At week 12, the treatment difference between PRALUENT 300 mg every 4 weeks and placebo in mean percent change in LDL-C from baseline was -54% (97.5% CI: -61%, -48%), and the treatment difference between PRALUENT 75 mg every 2 weeks and placebo in mean percent change in LDL-C was -44% (97.5% CI: -53%, -35%) (Figure 4).

Figure 4: Mean Percent Change from Baseline in LDL-C up to Week 12 in Adult Patients on Concomitant Statin Treated with PRALUENT 75 mg Every 2 Weeks, PRALUENT 300 mg Every 4 Weeks or Placebo [The means were estimated based on all randomized patients, with multiple imputation of missing data taking into account treatment adherence]

At week 12, if additional LDL-C lowering was required based on pre-specified LDL-C criteria, PRALUENT was adjusted to 150 mg every 2 weeks for the remainder of the trial. The dose was adjusted to 150 mg every 2 weeks in approximately 20% of patients treated with PRALUENT 75 mg every 2 weeks or 300 mg every 4 weeks for at least 12 weeks.

At week 24, the treatment difference between initial assignment to PRALUENT 300 mg every 4 weeks and placebo in mean percent change in LDL-C from baseline was -56% (97.5% CI: -62%, -49%; p-value: <0.0001), and the treatment difference between initial assignment to PRALUENT 75 mg every 2 weeks and placebo in mean percent change in LDL-C from baseline was -48% (97.5% CI: -57%, -39%).

In the cohort of patients not treated with a concomitant statin, the mean LDL-C at baseline was 142 mg/dL. The treatment difference between PRALUENT and placebo were similar to the cohort of patients treated with a concomitant statin.

The proportion of patients who discontinued trial drug prior to the 24-week primary endpoint was 12% among those treated with PRALUENT 300 mg every 4 weeks, 14% among those treated with PRALUENT 75 mg every 2 weeks, and 15% among those treated with placebo.

Trial 8 (ODYSSEY ESCAPE, NCT02326220) was a multicenter, double-blind, placebo-controlled trial that randomly assigned adult patients with HeFH who were undergoing LDL apheresis to PRALUENT 150 mg every 2 weeks (N=41) or placebo (N=21). Patients were treated in combination with their usual LDL apheresis schedule for 6 weeks.

Baseline Disease and Demographic Characteristics

The mean age was 59 years (range 27-79), 42% were female, 97% were White, 3% were Black or African American, and 0% identified as Hispanic or Latino ethnicity. The mean LDL-C at baseline, measured before the apheresis procedure, was 181 mg/dL.

Endpoint Results

At week 6, the mean percent change from baseline in pre-apheresis LDL-C was -53% in patients in the PRALUENT group compared to 1% in patients who received placebo.

The proportion of patients who discontinued study drug prior to the 6-week endpoint was 2% among those treated with PRALUENT 150 mg every 2 weeks and 5% among those treated with placebo.

Trial 9 (ODYSSEY COMBO II, NCT01644188) was a multicenter, double-blind, ezetimibe-controlled trial that randomly assigned 479 adult patients to PRALUENT 75 mg every 2 weeks/150 mg every 2 weeks and 241 adult patients to ezetimibe 10 mg/day. Patients were taking a maximally tolerated dose of a statin and required additional LDL-C reduction.

Baseline Disease and Demographic Characteristics

The mean age was 62 years (range 29-88), 26% were female, 85% were White, 4% were Black or African American, and 3% identified as Hispanic or Latino ethnicity. Mean baseline LDL-C was 107 mg/dL.

Endpoint Results

At week 12, the mean percent change from baseline in LDL-C was -50% with PRALUENT compared to -22% with ezetimibe, and the treatment difference between PRALUENT and ezetimibe in mean LDL-C percent change was -28% (95% CI: -32%, -23%).

At week 12, if additional LDL-C lowering was required based on pre-specified LDL-C criteria, PRALUENT was up-titrated to 150 mg every 2 weeks for the remainder of the trial. The dose was up-titrated to 150 mg every 2 weeks in 82 (18%) of 446 patients treated with PRALUENT for at least 12 weeks. At week 24, the mean percent change from baseline in LDL-C was -48% with PRALUENT and -20% with ezetimibe, and the treatment difference between PRALUENT and ezetimibe in mean LDL-C percent change was -28% (95% CI: -33%, -23%; p-value: <0.0001).

The proportion of patients who prematurely discontinued trial drug prior to the 24-week primary endpoint was 9% among those treated with PRALUENT and 10% among those treated with ezetimibe.

Trial 10 (ODYSSEY MONO, NCT01644474) was a multicenter, double-blind, ezetimibe-controlled trial in adult patients with a moderate CV risk, not taking statins or other lipid-modifying therapies, and a baseline LDL-C between 100 mg/dL to 190 mg/dL that randomly assigned 52 patients to PRALUENT 75 mg every 2 weeks and 51 patients to ezetimibe 10 mg/day.

Baseline Disease and Demographic Characteristics

The mean age was 60 years (range 45-72), 47% were female, 90% were White and 10% were Black or African American, and 1% identified as Hispanic or Latino ethnicity. Mean baseline LDL-C was 140 mg/dL.

Endpoint Results

At week 12, the mean percent change from baseline in LDL-C was -48% with PRALUENT compared to -19% with ezetimibe, and the treatment difference between PRALUENT 75 mg every 2 weeks and ezetimibe in mean LDL-C percent change was -29% (95% CI: -37%, -22%). At week 12, if additional LDL-C lowering was required based on pre-specified LDL-C criteria, PRALUENT was up-titrated to 150 mg every 2 weeks for the remainder of the trial. The dose was up-titrated to 150 mg every 2 weeks in 14 (30%) of 46 patients treated with PRALUENT for at least 12 weeks. At week 24, the mean percent change from baseline in LDL-C was -45% with PRALUENT and -14% with ezetimibe, and the treatment difference between PRALUENT and ezetimibe in mean LDL-C percent change was -31% (95% CI: -40%, -22%; p-value: <0.0001).

The proportion of patients who prematurely discontinued trial drug prior to the 24-week endpoint was 15% among those treated with PRALUENT and 14% among those treated with ezetimibe.

Adult Patients with HoFH

Trial 11 (ODYSSEY HoFH, NCT03156621) was a multicenter, double-blind, placebo-controlled trial that randomly assigned 45 adult patients to PRALUENT 150 mg every 2 weeks and 24 adult patients to placebo. Patients were taking maximally tolerated doses of statins with or without other lipid-lowering therapy and required additional LDL-C reduction.

Randomization was stratified by LDL apheresis treatment status. The diagnosis of HoFH was made by either clinical diagnosis, which included a history of an untreated total cholesterol concentration >500 mg/dL together with either xanthoma before 10 years of age or with a history of total cholesterol >250 mg in both parents, or by genetic testing.

Baseline Disease and Demographic Characteristics

The mean age was 43 years (range 19-81), 51% were female, 78% were White, 3% were Black or African American, 17% were Asian, and 3% identified as Hispanic or Latino ethnicity. Mean baseline LDL-C was 283 mg/dL with 97% on statins, 72% on ezetimibe, and 14% on lomitapide.

Endpoint Results

At week 12, the treatment difference between PRALUENT and placebo in mean LDL-C percent change from baseline was -36% (95% CI: -51% to -20%; p <0.0001) (see Figure 5). For the effect of PRALUENT on lipid parameters as compared to placebo, see Table 5. No patient discontinued from the trial prior to the 12-week primary endpoint.

Patients with two LDL-receptor negative alleles (little to no residual function) had a minimal to absent response to PRALUENT.

Figure 5: LS Mean Percent Change from Baseline in LDL-C Over 12 Weeks in Adult Patients with HoFH (ODYSSEY HoFH)

Table 5: Effect of PRALUENT on Lipid Parameters in Adult Patients with HoFH (LS Mean Percent Change from Baseline to Week 12 in ODYSSEY HoFH)
Treatment Group | LDL-C | Apo B | Non-HDL-C | Total Cholesterol
Placebo (n=24) | 9 | 7 | 8 | 7
PRALUENT 150 mg every 2 weeks (n=45) | -27 | -23 | -25 | -20
Difference from placebo (LS Mean) (95% CI) | -36 (-51, -20) | -30 (-42, -17) | -33 (-48, -18) | -27 (-39, -14)

14.3 Clinical Trials in Pediatric Patients with HeFH

Trial 12 (EFC14643, NCT03510884) was a randomized, multicenter, placebo controlled, double blind, 24 week trial in 153 pediatric patients aged 8 to 17 years with HeFH. Patients were on a low-fat diet and receiving background lipid-lowering therapy.

Patients were randomized in a 2:1 ratio to receive PRALUENT or placebo. In the PRALUENT group dosed every 2 weeks, 49 patients received a dose of 40 mg for body weight less than 50 kg or 75 mg for body weight 50 kg or more. The 40 mg dosage every 2 weeks is not approved [see Dosage and Administration (2.2)]. In the PRALUENT group dosed every 4 weeks, 52 patients received a dose of 150 mg for body weight less than 50 kg or 300 mg for body weight 50 kg or more. Dose adjustment of PRALUENT to 75 mg every 2 weeks for body weight less than 50 kg or 150 mg every 2 weeks for body weight 50 kg or more occurred at week 12 in patients with LDL-C ≥110 mg/dL.

Baseline Disease and Demographic Characteristics

The diagnosis of HeFH was made based on criteria from Simon Broome Register Group (1991) or by genetic testing. The mean age was 13 years (range: 8 to 17 years); 57% female; 82% White, 2% Black or African American, 10% American Indian or Alaska Native, and <1% not reported; 18% Hispanic/Latino ethnicity. Mean body weight was 53kg. The mean LDL-C at baseline was 174mg/dL; Of the patients receiving PRALUENT once every 2 weeks with an optional up-titration, 99% were on statins and 7% were on ezetimibe at baseline. Of the patients receiving PRALUENT once every 4 weeks with an optional up-titration, 91% were on statins and 20% were on ezetimibe at baseline.

Endpoint Results

At week 24 in the group receiving treatment every 4 weeks, the treatment difference between the PRALUENT and placebo groups in LS mean LDL-C percent change from baseline was -31.4% (97.5% CI: -45.0 to -17.9; p<0.0001) (see Table 6 and Figure 6). For the effect of PRALUENT on lipid parameters as compared to placebo see Table 6.

Figure 6: LDL-C LS Mean Percent Change from Baseline Over Time Through Week 24 in Pediatric Patients (aged 8 to 17 years) with HeFH Treated with PRALUENT Every 4 Weeks or Placebo [A pattern-mixture approach was used with multiple imputation of missing post-treatment values based on a patient's own baseline value and multiple imputation of missing on-treatment values based on a model including available on-treatment values]

b Number of patients with observed data

Table 6: Mean Percent Change from Baseline and Difference from Placebo in Lipid Parameters at Week 24 in Pediatric Patients (aged 8 to 17 years)
Treatment Group [The percent of missing data was 5% in the every 2 week group and 13% in the every 4 week group] | LDL-C | Apo B | Non-HDL-C | Total Cholesterol
PRALUENT once every 4 weeks (150 mg for body weight less than 50 kg or 300 mg for body weight 50 kg or more) [In the PRALUENT group 52 patients received a dose of 150 mg every 4 weeks (body weight less than 50 kg) or 300 mg every 4 weeks (body weight 50 kg or more). At week 12, a total of 15 (28.8%) patients had an automatic blinded dose adjustment to 75 mg every 2 weeks (body weight less than 50 kg) or 150 mg every 2 weeks (body weight 50 kg or more).]
LS Mean: Placebo (n=27) | -5.2 | -3.3 | -4.1 | -4.4
LS Mean: PRALUENT (n=52) | -36.6 | -33.0 | -34.2 | -26.7
LS Mean Difference from Placebo [A pattern-mixture approach was used with multiple imputation of missing post-treatment values based on a patient's own baseline value and multiple imputation of missing on-treatment values based on a model including available on-treatment values] (97.5% CI) | -31.4 (-45.0, -17.9) | -29.7 (-41.1, -18.2) | -30.1 (-43.0, -17.2) | -22.3 (-33.0, -11.6)
PRALUENT once every 2 weeks (40 mg for body weight less than 50 kg or 75 mg for body weight 50 kg or more) [In the PRALUENT group dosed every 2 weeks, 49 patients received a dose of 40 mg for body weight less than 50 kg or 75 mg for body weight 50 kg or more. At week 12, a total of 22 (44.9%) patients had an automatic blinded dose adjustment to 75 mg every 2 weeks (body weight less than 50 kg) or 150 mg every 2 weeks (body weight 50 kg or more).] , [The 40 mg dosage every 2 weeks is not approved]
LS Mean: Placebo (n=25) | 9.7 | 10.4 | 9.7 | 7.4
LS Mean: PRALUENT (n=49) | -31.9 | -25.7 | -29.5 | -22.4
LS Mean Difference from Placebo (97.5% CI) | -41.7 (-54.2, -29.1) | -36.2 (-45.8, -26.5) | -39.2 (-50.6, -27.8) | -29.8 (-38.7, -21.0)

16 HOW SUPPLIED/STORAGE AND HANDLING

PRALUENT injection is a clear, colorless to pale yellow solution, supplied as follows:

Strength | Package Size | NDC
75 mg/mL single-dose pre-filled pen | 1 pen | 61755-020-01
75 mg/mL single-dose pre-filled pen | 2 pens | 61755-020-02
150 mg/mL single-dose pre-filled pen | 1 pen | 61755-021-01
150 mg/mL single-dose pre-filled pen | 2 pens | 61755-021-02

The needle shield is not made with natural rubber latex.

STORAGE AND HANDLING

Store in a refrigerator at 36°F to 46°F (2°C to 8°C) in the original carton to protect from light. Do not freeze. Do not shake.

PRALUENT may be kept at room temperature up to 77°F (25°C) in the original carton for 30 days. If not used within the 30 days, discard PRALUENT.

17 PATIENT COUNSELING INFORMATION

Advise the patient to read the FDA-approved patient labeling (Patient Information and Instructions for Use).

Hypersensitivity Reactions

Inform patients that serious hypersensitivity reactions (e.g., angioedema) have been reported in patients treated with PRALUENT. Advise patients on the symptoms of hypersensitivity reactions and instruct them to discontinue PRALUENT and seek medical attention promptly, if such symptoms occur [see Warnings and Precautions (5.1)].

Administration

Provide guidance to patients and caregivers on proper subcutaneous injection technique and how to use the pre-filled pen. Inform patients that it may take up to 20 seconds to inject PRALUENT. Inform patients the pre-filled pen should be allowed to warm to room temperature for 30 to 40 minutes prior to use if refrigerated.

Pregnancy

Advise women who are exposed to PRALUENT during pregnancy that there is a pregnancy safety study that monitors pregnancy outcomes. Encourage these patients to report their pregnancy to Regeneron at 1 844-734-6643 [see Use in Specific Populations (8.1)].

Manufactured by:
Regeneron Pharmaceuticals, Inc.
Tarrytown, NY 10591
U.S. License # 1760

PRALUENT is a registered trademark of Regeneron Pharmaceuticals, Inc.

© 2025 Regeneron Pharmaceuticals, Inc. All rights reserved.

Patient Information
PRALUENT® (PRAHL-u-ent)
(alirocumab)
injection, for subcutaneous use

What is PRALUENT?
PRALUENT is an injectable prescription medicine used:

- to reduce the risk of major adverse cardiovascular (CV) events, such as death from coronary heart disease, heart attack, stroke, or certain types of chest pain conditions (unstable angina) requiring hospitalization, in adults at increased risk for these events.
- along with diet and exercise, to reduce low-density lipoprotein cholesterol (LDL-C) or bad cholesterol in:
  - adults with high blood cholesterol levels called hypercholesterolemia.
  - adults and children aged 8 years and older with a type of high cholesterol called heterozygous familial hypercholesterolemia (HeFH).
  - adults with a type of high cholesterol called homozygous familial hypercholesterolemia (HoFH).

It is not known if PRALUENT is safe and effective in children who are younger than 8 years of age or in children with other types of high cholesterol (hypercholesterolemia).

Who should not use PRALUENT?
Do not use PRALUENT if you are allergic to alirocumab or to any of the ingredients in PRALUENT. See the end of this leaflet for a complete list of ingredients in PRALUENT.

What should I tell my healthcare provider before using PRALUENT?
Before you start using PRALUENT, tell your healthcare provider about all of your medical conditions, including allergies, and if you:

- are pregnant or plan to become pregnant. It is not known if PRALUENT will harm your unborn baby. Tell your healthcare provider if you become pregnant while taking PRALUENT.
- are breastfeeding or plan to breastfeed. You and your healthcare provider should decide if you will take PRALUENT or breastfeed. You should not do both without talking to your healthcare provider first.

If you are pregnant during PRALUENT treatment, you are encouraged to call Regeneron at 1-844-734-6643 to share information about the health of you and your baby.
Tell your healthcare provider or pharmacist about all the medicines you take, including prescription and over-the-counter medicines, vitamins, and herbal supplements.

How should I use PRALUENT?

- See the detailed "Instructions for Use" that comes with this Patient Information about the right way to prepare and give your PRALUENT injections.
- Use PRALUENT exactly as your healthcare provider tells you to use it.
- PRALUENT comes as a single-dose (1 time) pre-filled pen (autoinjector). Your healthcare provider will prescribe the dosage that is best for you.
- If your healthcare provider decides that you or a caregiver can give the injections of PRALUENT, you or your caregiver should receive training on the right way to prepare and give PRALUENT. Do not try to inject PRALUENT until you have been shown the right way by your healthcare provider or nurse.
- In children aged 12 to 17 years, it is recommended that PRALUENT be given by or under the supervision of an adult. In children aged 8 to 11 years, PRALUENT should be given by a caregiver.
- PRALUENT is injected under the skin (subcutaneously) every 2 weeks or every 4 weeks (monthly).
- If your healthcare provider prescribes you the monthly dose, give 2 separate injections in a row, using a different pen for each injection and 2 different injection sites.
- Do not inject PRALUENT together with other injectable medicines at the same injection site.
- Always check the label of your pen to make sure you have the correct medicine and the correct dose of PRALUENT before each injection.
- If you forget to use PRALUENT or are not able to take the dose at your regular time, inject your missed dose as soon as you remember, within 7 days. Then, if you inject every 2 weeks take your next dose in 2 weeks from the day you missed your dose or if you inject every 4 weeks take your next dose in 4 weeks from the day you missed your dose. This will put you back on your original schedule.
- If you missed a dose by more than 7 days and you inject every 2 weeks wait until your next scheduled dose to re-start PRALUENT or if you inject every 4 weeks start a new schedule from the time you remember to take your dose.
  If you are not sure when to re-start PRALUENT, ask your healthcare provider or pharmacist.
- If you use more PRALUENT than you should, talk to your healthcare provider or pharmacist.
- Do not stop using PRALUENT without talking with your healthcare provider. If you stop using PRALUENT, your cholesterol levels can increase.

What are the possible side effects of PRALUENT?
PRALUENT can cause serious side effects, including:

- allergic reactions. PRALUENT may cause allergic reactions that can be severe and require treatment in a hospital. Stop using PRALUENT and call your healthcare provider or go to the nearest hospital emergency room right away if you have any symptoms of an allergic reaction including:

- a severe rash
- redness
- hives

- severe itching
- trouble breathing

- swelling of the face, lips, throat or tongue

The most common side effects of PRALUENT include:

- redness, itching, swelling, pain, or tenderness at the injection site

- flu
- muscle pain

Tell your healthcare provider if you have any side effect that bothers you or that does not go away.
These are not all of the possible side effects of PRALUENT. Ask your healthcare provider or pharmacist for more information.
Call your doctor for medical advice about side effects. You may report side effects to FDA at 1-800-FDA-1088.

General information about the safe and effective use of PRALUENT.
Medicines are sometimes prescribed for purposes other than those listed in a Patient Information leaflet. Do not use PRALUENT for a condition for which it was not prescribed. Do not give PRALUENT to other people, even if they have the same symptoms that you have. It may harm them.
This Patient Information summarizes the most important information about PRALUENT. If you would like more information, talk with your healthcare provider. You can ask your pharmacist or healthcare provider for information about PRALUENT that is written for health professionals.
For more information about PRALUENT, go to www.PRALUENT.com or call 1-844-PRALUENT (1-844-772-5836).

What are the ingredients in PRALUENT?

- Active ingredient: alirocumab

- Inactive ingredients: histidine, polysorbate 20, sucrose, and Water for Injection, USP.

Manufactured by: Regeneron Pharmaceuticals, Inc. Tarrytown, NY 10591, U.S. License # 1760; PRALUENT is a registered trademark of Regeneron Pharmaceuticals, Inc. / ©2025 Regeneron Pharmaceuticals, Inc. All rights reserved.

This Patient Information has been approved by the U.S. Food and Drug Administration.

Revised: October 2025

Instructions For Use
PRALUENT® (PRAHL-u-ent)
(alirocumab)
Injection, for Subcutaneous Injection
Single-Dose Pre-Filled Pen (75 mg/mL)

Important Information

- The device is a single-dose disposable pen. It contains 75 mg of PRALUENT (alirocumab) in 1 mL.
- The PRALUENT pen contains medicine prescribed by your healthcare provider.
- The medicine is injected under your skin and can be given by yourself or someone else (caregiver).
- It is important that you do not try to give yourself or someone else the injection unless you have received training from your healthcare provider.
- In children aged 8 to 11 years, PRALUENT must be given by a caregiver.
- In children aged 12 to 17 years, it is recommended that PRALUENT be givenby or under supervision of an adult.

- This pen can only be used for 1 single injection, and must be thrown away (discarded) after use.
- Read all of the instructions carefully before using the PRALUENT pen.
- Follow these instructions every time you use a PRALUENT pen.
- Do not touch the yellow safety cover.
- Do not use the pen if it has been dropped or damaged.
- Do not use the pen if the blue cap is missing or not securely attached.
- Do not re-use a pen.

Storage of PRALUENT

- Store unused pens in the refrigerator between 36°F to 46°F (2°C to 8°C) in the original carton to protect from light.
- Do not freeze.
- Do not expose the pen to extreme heat or direct sunlight.
- Do not shake.
- PRALUENT should be allowed to warm to room temperature for 30 to 40 minutes before use.
- If needed, PRALUENT may be kept at room temperature up to 77°F (25°C) for 30 days in the original carton to protect from light. Do not store above 77°F (25°C).
- After PRALUENT is removed from the refrigerator it must be used within 30 days or thrown away.
- Keep the PRALUENT pens and all medicines out of the reach of children.

Keep this leaflet. If you have questions, ask your healthcare provider or call 1-844-PRALUENT (1-844-772-5836).

The parts of the PRALUENT pen are shown in this picture.

Step A: Getting ready for your injection.

Before you start you will need:

- the PRALUENT pen
- 1 alcohol wipe
- 1 cotton ball or gauze
- a sharps container or a puncture-resistant container (see Step B8)

A1: Look at the label on the pen.

- Check that you have the correct product and the correct dose.
- Check the expiration date (EXP): do not use if this date has passed.

A2: Look at the window.

- Check the liquid is clear, colorless to pale yellow and free from particles (see Figure A).
- You may see air bubbles. This is normal.
- Do not use if the window appears solid yellow (see Figure B).
- Do not use this medicine if the solution is discolored or cloudy, or if it contains visible flakes or particles.

A3: Let the pen warm up at room temperature for 30 to 40 minutes.

- This is important for administering the entire dose and helps minimize discomfort.
- Take PRALUENT out of the refrigerator to warm up before using.
- Do not heat the pen, let it warm up on its own.
- Do not put the pen back in the refrigerator.

A4: Prepare the injection site.

- Wash your hands with soap and water and dry with a towel.
- Clean skin in the injection area with an alcohol wipe.
- You can inject into your (see picture):
  - thighs
  - stomach (except for the 2 inch area around your belly button)
  - upper arms
- You can stand or sit to give yourself an injection.

Important:

- Change (rotate) your injection site each time you give yourself an injection. If you need to use the same injection site, make sure it is not the same spot on the site you used last time.
- Do not inject into areas where the skin is tender, bruised, hard, or red. Do not inject PRALUENT into areas with visible veins, scars or stretch marks.

Step B: How to give your injection.

B1: After completing all steps in "Step A: Getting ready for your injection", pull off the blue cap.

- Do not pull off the cap until you are ready to inject.
- Do not put the blue cap back on.

B2: Hold the PRALUENT pen like this.

- Do not touch the yellow safety cover.
- Make sure you can see the window.

B3: Press the yellow safety cover on your skin at roughly a 90° angle.

- For children younger than 12 years of age, pinching the skin before and during the injection is required.
- In adults and children aged 12 years and older, pinching of skin may be required to make the injection site firm.
- Press and firmly hold the pen against your body until the yellow safety cover is no longer visible. The pen will not work if the yellow safety cover is not depressed fully.

B4: Push and immediately release the green button with your thumb.

- You will hear a click. Your injection has now started.
- The window will start to turn yellow.

B5: Keep holding the pen against your skin after releasing the button.

- The injection may take up to 20 seconds.

B6: Check the window has turned yellow, before removing the pen.

- Do not remove the pen until the entire window has turned yellow.
- Your injection is complete when the window has turned completely yellow, you may hear a second click.
- If the window does not turn completely yellow, call 1-844-772-5836 for help. Do not give yourself a second dose without speaking to your healthcare provider.

B7: Pull pen away from your skin.

- Do not rub the skin after the injection.
- If you see any blood, press a cotton ball or gauze on the site until the bleeding stops.

B8: Throw away (Discard) pen and cap.

- Do not put the blue cap back on.
- Throw away pen and cap in a puncture-resistant container immediately after they have been used.

Disposing of used pens:

- Put your used pens in a FDA-cleared sharps disposal container right away after use. Do not throw away (dispose of) pens and caps in your household trash.
- If you do not have a FDA-cleared sharps disposal container, you may use a household container that is:
  - made of a heavy-duty plastic,
  - can be closed with a tight-fitting, puncture-resistant lid, without sharps being able to come out,
  - upright and stable during use,
  - leak-resistant, and
  - properly labeled to warn of hazardous waste inside the container.
- When your sharps disposal container is almost full, you will need to follow your community guidelines for the right way to dispose of your sharps disposal container. There may be state or local laws about how you should throw away used needles and syringes. For more information about safe sharps disposal, and for specific information about sharps disposal in the state that you live in, go to the FDA's website at: http://www.fda.gov/safesharpsdisposal.
- Do not dispose of your used sharps disposal container in your household trash unless your community guidelines permit this. Do not recycle your used sharps disposal container.

Keep PRALUENT and all medicines out of the reach of children.

This Instructions for Use has been approved by the U.S. Food and Drug Administration.

Manufactured by:
Regeneron Pharmaceuticals, Inc.
Tarrytown, NY 10591
U.S. License # 1760

PRALUENT is a registered trademark of Regeneron Pharmaceuticals, Inc.

©2024 Regeneron Pharmaceuticals, Inc. All rights reserved.

Revised: March 2024

Instructions For Use
PRALUENT® (PRAHL-u-ent)
(alirocumab)
Injection, for Subcutaneous Injection
Single-Dose Pre-Filled Pen (150 mg/mL)

Important Information

- The device is a single-dose disposable pen. It contains 150 mg of PRALUENT (alirocumab) in 1 mL.
- The PRALUENT pen contains medicine prescribed by your healthcare provider.
- The medicine is injected under your skin and can be given by yourself or someone else (caregiver).
- It is important that you do not try to give yourself or someone else the injection unless you have received training from your healthcare provider.
- In children aged 8 to 11 years, PRALUENT must be given by a caregiver.
- In children aged 12 to 17 years, it is recommended that PRALUENT be given by or under supervision of an adult.

- This pen can only be used for 1 single injection, and must be thrown away (discarded) after use.
- Read all of the instructions carefully before using the PRALUENT pen.
- Follow these instructions every time you use a PRALUENT pen.
- Do not touch the yellow safety cover.
- Do not use the pen if it has been dropped or damaged.
- Do not use the pen if the blue cap is missing or not securely attached.
- Do not re-use a pen.

Storage of PRALUENT

- Store unused pens in the refrigerator between 36°F to 46°F (2°C to 8°C) in the original carton to protect from light.
- Do not freeze.
- Do not expose the pen to extreme heat or direct sunlight.
- Do not shake.
- PRALUENT should be allowed to warm to room temperature for 30 to 40 minutes before use.
- If needed, PRALUENT may be kept at room temperature up to 77°F (25°C) for 30 days in the original carton to protect from light. Do not store above 77°F (25°C).
- After PRALUENT is removed from the refrigerator it must be used within 30 days or thrown away.
- Keep the PRALUENT pens and all medicines out of the reach of children.

Keep this leaflet. If you have questions, ask your healthcare provider or call 1-844-PRALUENT (1-844-772-5836).

The parts of the PRALUENT pen are shown in this picture.

Step A: Getting ready for your injection.

Before you start you will need:

- the PRALUENT pen
- 1 alcohol wipe
- 1 cotton ball or gauze
- a sharps container or a puncture-resistant container (see Step B8)

A1: Look at the label on the pen.

- Check that you have the correct product and the correct dose.
- Check the expiration date (EXP): do not use if this date has passed.

A2: Look at the window.

- Check the liquid is clear, colorless to pale yellow and free from particles (see Figure A).
- You may see air bubbles. This is normal.
- Do not use if the window appears solid yellow (see Figure B).
- Do not use this medicine if the solution is discolored or cloudy, or if it contains visible flakes or particles.

A3: Let the pen warm up at room temperature for 30 to 40 minutes.

- This is important for administering the entire dose and helps minimize discomfort.
- Take PRALUENT out of the refrigerator to warm up before using.
- Do not heat the pen, let it warm up on its own.
- Do not put the pen back in the refrigerator.

A4: Prepare the injection site.

- Wash your hands with soap and water and dry with a towel.
- Clean skin in the injection area with an alcohol wipe.
- You can inject into your (see picture):
  - thighs
  - stomach (except for the 2 inch area around your belly button)
  - upper arms
- You can stand or sit to give yourself an injection.

Important:

- Change (rotate) your injection site each time you give yourself an injection. If you need to use the same injection site, make sure it is not the same spot on the site you used last time.
- Do not inject into areas where the skin is tender, bruised, hard, or red. Do not inject PRALUENT into areas with visible veins, scars or stretch marks.

Step B: How to give your injection.

B1: After completing all steps in "Step A: Getting ready for your injection", pull off the blue cap.

- Do not pull off the cap until you are ready to inject.
- Do not put the blue cap back on.

B2: Hold the PRALUENT pen like this.

- Do not touch the yellow safety cover.
- Make sure you can see the window.

B3: Press the yellow safety cover on your skin at roughly a 90° angle.

- For children younger than 12 years of age, pinching the skin before and during the injection is required.
- In adults and children aged 12 years and older, pinching of skin may be required to make the injection site firm.
- Press and firmly hold the pen against your body until the yellow safety cover is no longer visible. The pen will not work if the yellow safety cover is not depressed fully.

B4: Push and immediately release the gray button with your thumb.

- You will hear a click. Your injection has now started.
- The window will start to turn yellow.

B5: Keep holding the pen against your skin after releasing the button.

- The injection may take up to 20 seconds.

B6: Check the window has turned yellow, before removing the pen.

- Do not remove the pen until the entire window has turned yellow.
- Your injection is complete when the window has turned completely yellow, you may hear a second click.
- If the window does not turn completely yellow, call 1-844-772-5836 for help. Do not give yourself a second dose without speaking to your healthcare provider.

B7: Pull pen away from your skin.

- Do not rub the skin after the injection.
- If you see any blood, press a cotton ball or gauze on the site until the bleeding stops.

B8: Throw away (Discard) pen and cap.

- Do not put the blue cap back on.
- Throw away pen and cap in a puncture-resistant container immediately after they have been used.

Disposing of used pens:

- Put your used pens in a FDA-cleared sharps disposal container right away after use. Do not throw away (dispose of) pens and caps in your household trash.
- If you do not have a FDA-cleared sharps disposal container, you may use a household container that is:
  - made of a heavy-duty plastic,
  - can be closed with a tight-fitting, puncture-resistant lid, without sharps being able to come out,
  - upright and stable during use,
  - leak-resistant, and
  - properly labeled to warn of hazardous waste inside the container.
- When your sharps disposal container is almost full, you will need to follow your community guidelines for the right way to dispose of your sharps disposal container. There may be state or local laws about how you should throw away used needles and syringes. For more information about safe sharps disposal, and for specific information about sharps disposal in the state that you live in, go to the FDA's website at: http://www.fda.gov/safesharpsdisposal.
- Do not dispose of your used sharps disposal container in your household trash unless your community guidelines permit this. Do not recycle your used sharps disposal container.

Keep PRALUENT and all medicines out of the reach of children.

This Instructions for Use has been approved by the U.S. Food and Drug Administration.

Manufactured by:
Regeneron Pharmaceuticals, Inc.
Tarrytown, NY 10591
U.S. License # 1760

PRALUENT is a registered trademark of Regeneron Pharmaceuticals, Inc.

©2024 Regeneron Pharmaceuticals, Inc. All rights reserved.

Revised: March 2024

PRINCIPAL DISPLAY PANEL - 75 mg/mL Pen Carton

NDC 61755-020-02
Rx ONLY

75 mg/mL

Praluent®
alirocumab
Injection
75 mg/mL
Two Pre-filled Pens

For subcutaneous injection only. Single-dose.

Carton contains: Two single-dose pre-filled pens, the Package Insert,
Patient Information, and Instructions for Use.

OPEN
HERE

REGENERON

PRINCIPAL DISPLAY PANEL - 150 mg/mL Pen Carton

NDC 61755-021-02
Rx ONLY

150 mg/mL

Praluent®
alirocumab
Injection
150 mg/mL
Two Pre-filled Pens

For subcutaneous injection only. Single-dose.

Carton contains: Two single-dose pre-filled pens, the Package Insert,
Patient Information, and Instructions for Use.

OPEN
HERE

REGENERON